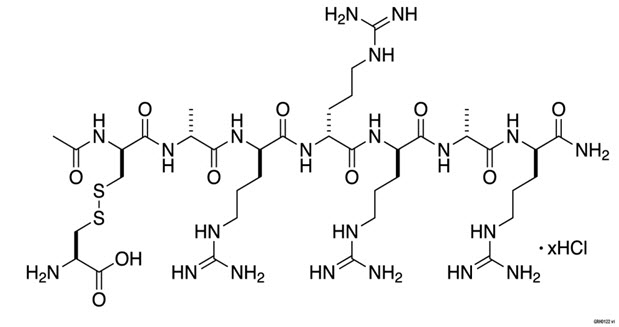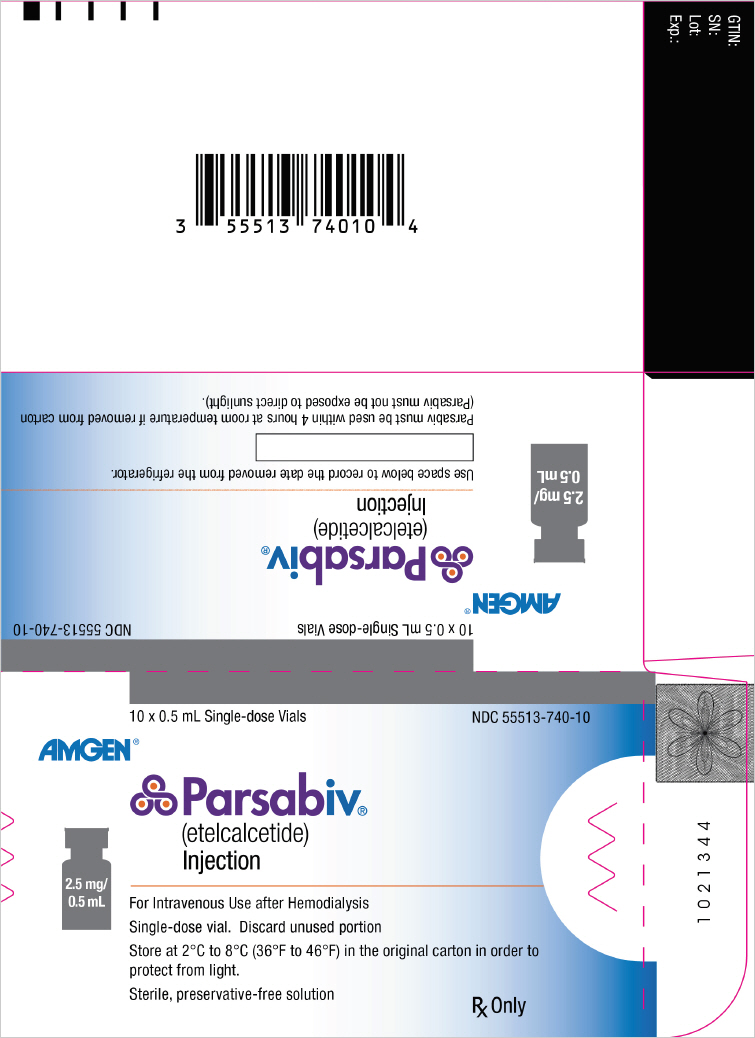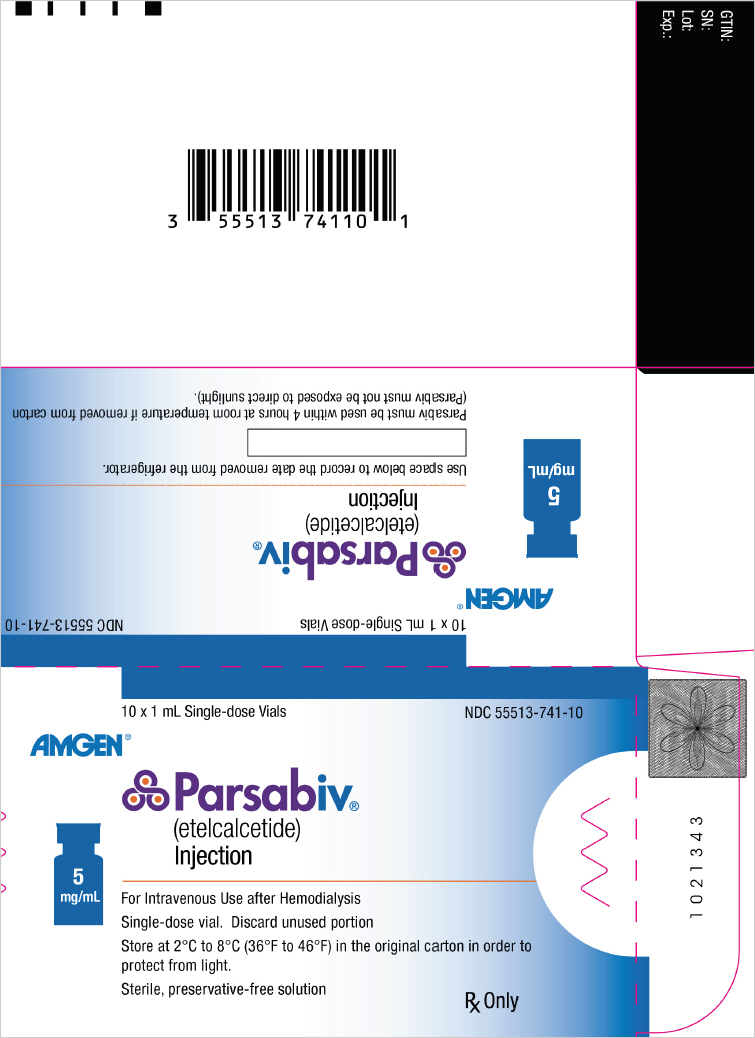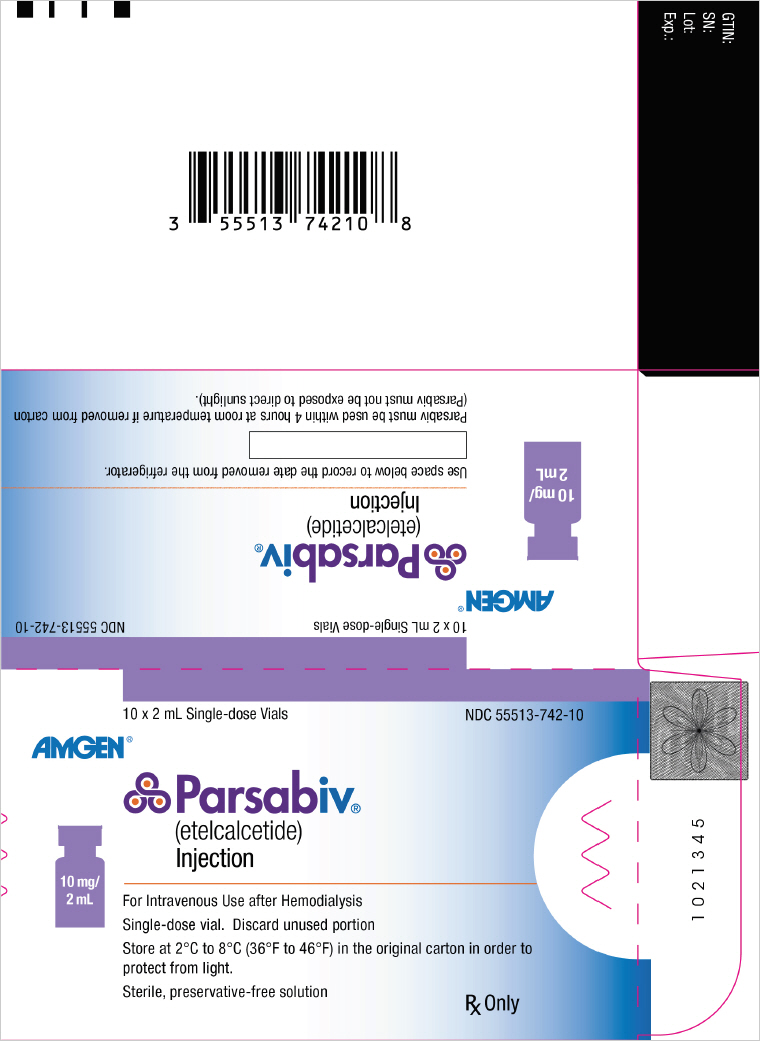 DRUG LABEL: PARSABIV
NDC: 55513-740 | Form: INJECTION, SOLUTION
Manufacturer: Amgen Inc
Category: prescription | Type: HUMAN PRESCRIPTION DRUG LABEL
Date: 20250110

ACTIVE INGREDIENTS: ETELCALCETIDE HYDROCHLORIDE 2.5 mg/0.5 mL
INACTIVE INGREDIENTS: SODIUM CHLORIDE 4.3 mg/0.5 mL; SUCCINIC ACID 0.6 mg/0.5 mL; SODIUM HYDROXIDE; HYDROCHLORIC ACID

HIGHLIGHTS OF PRESCRIBING INFORMATION

These highlights do not include all the information needed to use PARSABIV safely and effectively. See full prescribing information for PARSABIV.
PARSABIV® (etelcalcetide) injection, for intravenous use
Initial U.S. Approval: 2017

1 INDICATIONS AND USAGE

PARSABIV is a calcium-sensing receptor agonist indicated for:

- Secondary hyperparathyroidism (HPT) in adult patients with chronic kidney disease (CKD) on hemodialysis. (1)

Limitations of Use:

PARSABIV has not been studied in adult patients with parathyroid carcinoma, primary hyperparathyroidism, or with CKD who are not on hemodialysis and is not recommended for use in these populations.

2 DOSAGE AND ADMINISTRATION

- Ensure corrected serum calcium is at or above the lower limit of normal prior to initiation, dose increase, or re-initiation. (2.1)
- The recommended starting dose is 5 mg administered by intravenous bolus injection three times per week at the end of hemodialysis treatment. (2.1)
- The maintenance dose is individualized and determined by titration based on parathyroid hormone (PTH) and corrected serum calcium response. The dose range is 2.5 to 15 mg three times per week. (2.1)
- The dose may be increased in 2.5 mg or 5 mg increments no more frequently than every 4 weeks. (2.2)
- Measure serum calcium within 1 week after initiation or dose adjustment and every 4 weeks for maintenance. (2.2)
- Measure PTH after 4 weeks from initiation or dose adjustment. (2.2)
- Decrease or temporarily discontinue PARSABIV in individuals with PTH levels below the target range. (2.2)
- Consider decreasing or temporarily discontinuing PARSABIV or use concomitant therapies to increase corrected serum calcium in patients with a corrected serum calcium below the lower limit of normal but at or above 7.5 mg/dL without symptoms of hypocalcemia. (2.2)
- Stop PARSABIV and treat hypocalcemia if the corrected serum calcium falls below 7.5 mg/dL or patients report symptoms of hypocalcemia. (2.2)
- Do not mix or dilute prior to administration. (2.3)
- Administer by intravenous bolus injection into the venous line of the dialysis circuit after hemodialysis, during rinse back or intravenously after rinse back.
  - Administer a sufficient volume of saline, e.g. 150 mL of rinse back, after injection into the dialysis tubing.
  - If administered after rinse back, administer PARSABIV intravenously followed by at least 10 mL of saline flush. (2.3)

3 DOSAGE FORMS AND STRENGTHS

- Injection: 2.5 mg/0.5 mL solution in a single-dose vial (3)
- Injection: 5 mg/mL solution in a single-dose vial (3)
- Injection: 10 mg/2 mL solution in a single-dose vial (3)

4 CONTRAINDICATIONS

PARSABIV is contraindicated in patients with known hypersensitivity to etelcalcetide or any of its excipients. (4)

5 WARNINGS AND PRECAUTIONS

- Hypocalcemia: Sometimes severe. Severe hypocalcemia can cause paresthesias, myalgias, muscle spasms, seizures, QT prolongation, and ventricular arrhythmias. Patients predisposed to QT interval prolongation, ventricular arrhythmias, and seizures may be at increased risk and require close monitoring. Educate patients on the symptoms of hypocalcemia and advise them to contact a healthcare provider if they occur. (5.1)
- Worsening Heart Failure: Reductions in corrected serum calcium may be associated with congestive heart failure, however, a causal relationship to PARSABIV could not be completely excluded. Closely monitor patients for worsening signs and symptoms of heart failure. (5.2)
- Upper Gastrointestinal (GI) Bleeding: Patients with risk factors for upper GI bleeding may be at increased risk. Monitor patients and promptly evaluate and treat any suspected GI bleeding. (5.3)
- Adynamic Bone: May develop if PTH levels are chronically suppressed. If PTH levels decrease below the recommended target range, the dose of PARSABIV should be reduced or discontinued. (5.4)

6 ADVERSE REACTIONS

The most common adverse reactions (≥ 5%) were blood calcium decreased, muscle spasms, diarrhea, nausea, vomiting, headache, hypocalcemia, and paresthesia. (6)

To report SUSPECTED ADVERSE REACTIONS, contact Amgen Inc. at 1-800-77-AMGEN (1-800-772-6436) or FDA at 1-800-FDA-1088 or www.fda.gov/medwatch.

8 USE IN SPECIFIC POPULATIONS

Lactation: PARSABIV is not recommended when breastfeeding. (8.2)

FULL PRESCRIBING INFORMATION

1 INDICATIONS AND USAGE

PARSABIV is indicated for the treatment of secondary hyperparathyroidism (HPT) in adult patients with chronic kidney disease (CKD) on hemodialysis.

Limitations of Use:

PARSABIV has not been studied in adult patients with parathyroid carcinoma, primary hyperparathyroidism, or with chronic kidney disease who are not on hemodialysis and is not recommended for use in these populations.

2 DOSAGE AND ADMINISTRATION

2.1 Recommended Dosing

- Ensure corrected serum calcium is at or above the lower limit of normal prior to PARSABIV initiation, a PARSABIV dose increase, or re-initiation of PARSABIV therapy after a dosing interruption [see Dosage and Administration (2.2) and Warnings and Precautions (5.1)].
- The recommended starting dose of PARSABIV is 5 mg administered by intravenous (IV) bolus injection three times per week at the end of hemodialysis treatment [see Dosage and Administration (2.3)].
- The maintenance dose of PARSABIV is individualized and determined by titration based on parathyroid hormone (PTH) and corrected serum calcium response [see Dosage and Administration (2.2)]. The maintenance dose is the dose that maintains PTH levels within the recommended target range and corrected serum calcium within the normal range. The lowest maintenance dose of PARSABIV is 2.5 mg three times per week, and the highest maintenance dose of PARSABIV is 15 mg three times per week.
- Administer PARSABIV only at the end of hemodialysis treatment.
- If a regularly scheduled hemodialysis treatment is missed, DO NOT administer any missed doses. Resume PARSABIV at the end of the next hemodialysis treatment at the prescribed dose. If doses of PARSABIV are missed for more than 2 weeks, re-initiate PARSABIV at the recommended starting dose of 5 mg (or 2.5 mg if that was the patient's last dose).

2.2 Monitoring and Dose Adjustment

- Monitor corrected serum calcium and PTH levels during dose initiation, dose adjustment, and dose maintenance according to the schedule in Table 1.

Table 1: Recommended Schedule for Monitoring Corrected Serum Calcium and Parathyroid Hormone Levels during PARSABIV Treatment
 | Dose Initiation or Dose Adjustment | Maintenance
Corrected Serum Calcium Levels | 1 week after | Every 4 weeks
Parathyroid Hormone Levels | 4 weeks after | Per clinical practice

- Titrate PARSABIV dose based on PTH and corrected serum calcium response. At the maintenance dose, PTH levels should be within the recommended target range and corrected serum calcium within the normal range.
- Increase the dose of PARSABIV in 2.5 mg or 5 mg increments in individuals with corrected serum calcium within the normal range and PTH levels above the recommended target range based on the patient's PTH levels no more frequently than every 4 weeks up to a maximum dose of 15 mg three times per week.
- Decrease or temporarily discontinue PARSABIV dosing in individuals with PTH levels below the target range. In individuals with a corrected serum calcium below the lower limit of normal but at or above 7.5 mg/dL without symptoms of hypocalcemia, consider decreasing or temporarily discontinuing PARSABIV or use concomitant therapies to increase corrected serum calcium [see Warnings and Precautions (5.1)]. If the dose is stopped, then re-initiate PARSABIV at a lower dose when the PTH is within the target range and hypocalcemia has been corrected.
- Stop PARSABIV and treat hypocalcemia if the corrected serum calcium falls below 7.5 mg/dL or patients report symptoms of hypocalcemia [see Warnings and Precautions (5.1)]. When the corrected serum calcium is within normal limits, symptoms of hypocalcemia have resolved, and predisposing factors for hypocalcemia have been addressed, re-initiate PARSABIV at a dose 5 mg lower than the last administered dose. If the last administered dose of PARSABIV was 2.5 mg or 5 mg, re-initiate at a dose of 2.5 mg.

2.3 Administration

- Do not mix or dilute PARSABIV prior to administration. The solution is clear and colorless. Inspect PARSABIV for particulate matter and discoloration prior to administration. Do not use PARSABIV vials if particulate matter or discoloration is observed.
- PARSABIV is removed by the dialyzer membrane and must be administered after blood is no longer circulating through the dialyzer.
- Administer PARSABIV by intravenous bolus injection into the venous line of the dialysis circuit after hemodialysis during rinse back or intravenously after rinse back.
  - Administer a sufficient volume of saline, e.g. 150 mL of rinse back, after PARSABIV injection into the dialysis tubing.
  - If PARSABIV is administered after rinse back, administer PARSABIV intravenously followed by at least 10 mL of saline flush.

2.4 Switching from Cinacalcet to PARSABIV

- Discontinue cinacalcet for at least 7 days prior to starting PARSABIV, and initiate PARSABIV treatment at a starting dose of 5 mg. Ensure corrected serum calcium is at or above the lower limit of normal prior to PARSABIV initiation [see Warnings and Precautions (5.1)].

3 DOSAGE FORMS AND STRENGTHS

PARSABIV is a single-dose, clear, and colorless solution available as follows:

- Injection: 2.5 mg/0.5 mL solution in a single-dose vial
- Injection: 5 mg/mL solution in a single-dose vial
- Injection: 10 mg/2 mL solution (5 mg/mL) in a single-dose vial

4 CONTRAINDICATIONS

Hypersensitivity

PARSABIV is contraindicated in patients with known hypersensitivity to etelcalcetide or any of its excipients. Hypersensitivity reactions, including face edema and anaphylactic reaction, have occurred with PARSABIV [see Adverse Reactions (6)].

5 WARNINGS AND PRECAUTIONS

5.1 Hypocalcemia

PARSABIV lowers serum calcium [see Adverse Reactions (6.1)] and can lead to hypocalcemia, sometimes severe. Significant lowering of serum calcium can cause paresthesias, myalgias, muscle spasms, seizures, QT interval prolongation, and ventricular arrhythmia.

QT Interval Prolongation and Ventricular Arrhythmia

In the combined placebo-controlled studies, more patients treated with PARSABIV experienced a maximum increase from baseline of greater than 60 msec in the QTcF interval (0% placebo versus 1.2% PARSABIV). In these studies, the incidence of a maximum post-baseline predialysis QTcF > 500 msec in the placebo and PARSABIV groups was 1.9% and 4.8%, respectively [see Adverse Reactions (6.1)]. Patients with congenital long QT syndrome, history of QT interval prolongation, family history of long QT syndrome or sudden cardiac death, and other conditions that predispose to QT interval prolongation and ventricular arrhythmia may be at increased risk for QT interval prolongation and ventricular arrhythmias if they develop hypocalcemia due to PARSABIV. Closely monitor corrected serum calcium and QT interval in patients at risk receiving PARSABIV.

Seizures

Significant reductions in corrected serum calcium may lower the threshold for seizures. Patients with a history of seizure disorder may be at increased risk for seizures if they develop hypocalcemia due to PARSABIV. Monitor corrected serum calcium in patients with seizure disorders receiving PARSABIV.

Risk of Hypocalcemia with Other Serum Calcium Lowering Products

Concurrent administration of PARSABIV with another oral calcium-sensing receptor agonist could result in severe, life-threatening hypocalcemia. Patients switching from cinacalcet to PARSABIV should discontinue cinacalcet for at least 7 days prior to initiating PARSABIV [see Dosage and Administration (2.4)]. Closely monitor corrected serum calcium in patients receiving PARSABIV and concomitant therapies known to lower serum calcium.

Monitoring Serum Calcium and Patient Education

Measure corrected serum calcium prior to initiation of PARSABIV. Do not initiate in patients if the corrected serum calcium is less than the lower limit of normal. Monitor corrected serum calcium within 1 week after initiation or dose adjustment and every 4 weeks during treatment with PARSABIV [see Dosage and Administration (2.2)]. Educate patients on the symptoms of hypocalcemia and advise them to contact a healthcare provider if they occur.

Management of Hypocalcemia

If corrected serum calcium falls below the lower limit of normal or symptoms of hypocalcemia develop, start or increase calcium supplementation (including calcium, calcium-containing phosphate binders, and/or vitamin D sterols or increases in dialysate calcium concentration). PARSABIV dose reduction or discontinuation of PARSABIV may be necessary [see Dosage and Administration (2.2)].

5.2 Worsening Heart Failure

In clinical studies with PARSABIV, cases of hypotension, congestive heart failure, and decreased myocardial performance have been reported. In clinical studies, heart failure requiring hospitalization occurred in 2% of PARSABIV-treated patients and 1% of placebo-treated patients. Reductions in corrected serum calcium may be associated with congestive heart failure, however, a causal relationship to PARSABIV could not be completely excluded. Closely monitor patients treated with PARSABIV for worsening signs and symptoms of heart failure.

5.3 Upper Gastrointestinal Bleeding

In clinical studies, two patients treated with PARSABIV in 1253 patient-years of exposure had upper gastrointestinal (GI) bleeding noted at the time of death while no patient in the control groups in 384 patient-years of exposure had upper GI bleeding noted at the time of death. The exact cause of GI bleeding in these patients is unknown, and there were too few cases to determine whether these cases were related to PARSABIV.

Patients with risk factors for upper GI bleeding (such as known gastritis, esophagitis, ulcers, or severe vomiting) may be at increased risk for GI bleeding while receiving PARSABIV treatment. Monitor patients for worsening of common GI adverse reactions of nausea and vomiting associated with PARSABIV [see Adverse Reactions (6.1)] and for signs and symptoms of GI bleeding and ulcerations during PARSABIV therapy. Promptly evaluate and treat any suspected GI bleeding.

5.4 Adynamic Bone

Adynamic bone may develop if PTH levels are chronically suppressed. If PTH levels decrease below the recommended target range, the dose of vitamin D sterols and/or PARSABIV should be reduced or therapy discontinued. After discontinuation, resume therapy at a lower dose to maintain PTH levels in the target range [see Dosage and Administration (2.1)].

6 ADVERSE REACTIONS

The following adverse reactions are discussed in greater detail in other sections of the labeling:

- Hypocalcemia [see Warnings and Precautions (5.1)]
- Worsening Heart Failure [see Warnings and Precautions (5.2)]
- Upper Gastrointestinal Bleeding [see Warnings and Precautions (5.3)]
- Adynamic Bone [see Warnings and Precautions (5.4)]

6.1 Clinical Trials Experience

Because clinical trials are conducted under widely varying conditions, adverse reaction rates observed in the clinical trials of a drug cannot be directly compared with rates in the clinical trials of another drug and may not reflect the rates observed in clinical practice.

The data in Table 2 are derived from two placebo-controlled clinical studies in patients with chronic kidney disease and secondary hyperparathyroidism on hemodialysis. The data reflect exposure of 503 patients to PARSABIV with a mean duration of exposure to PARSABIV of 23.6 weeks. The mean age of patients was approximately 58 years, and 60% of the patients were male. Of the total patients, 67% were Caucasian, 28% were Black or African American, 2.6% were Asian, 1.2% were Native Hawaiian or Other Pacific Islander, and 1.6% were categorized as Other.

Table 2 shows common adverse reactions associated with the use of PARSABIV in the pool of placebo-controlled studies. These adverse reactions occurred more commonly on PARSABIV than on placebo and were reported in at least 5% of patients treated with PARSABIV.

Table 2: Adverse Reactions Reported in ≥ 5% of PARSABIV-Treated Patients
Adverse Reaction [Included adverse reactions reported with at least 1% greater incidence in the PARSABIV group compared to the placebo group] | Placebo (N = 513) | PARSABIV (N = 503)
Blood calcium decreased [Asymptomatic reductions in calcium below 7.5 mg/dL or clinically significant asymptomatic reductions in corrected serum calcium between 7.5 and < 8.3 mg/dL (that required medical management)] | 10% | 64%
Muscle spasms | 7% | 12%
Diarrhea | 9% | 11%
Nausea | 6% | 11%
Vomiting | 5% | 9%
Headache | 6% | 8%
Hypocalcemia [Symptomatic reductions in corrected serum calcium < 8.3 mg/dL] | 0.2% | 7%
Paresthesia [Paresthesia includes preferred terms of paresthesia and hypoesthesia] | 1% | 6%

Other adverse reactions associated with the use of PARSABIV but reported in < 5% of patients in the PARSABIV group in the two placebo-controlled clinical studies were:

- Hyperkalemia: 3% and 4% for placebo and PARSABIV, respectively.
- Hospitalization for Heart Failure: 1% and 2% for placebo and PARSABIV, respectively.
- Myalgia: 0.2% and 2% for placebo and PARSABIV, respectively.
- Hypophosphatemia: 0.2% and 1% for placebo and PARSABIV, respectively.

Description of Selected Adverse Reactions

Hypocalcemia

In the combined placebo-controlled studies, a higher proportion of patients on PARSABIV developed at least one corrected serum calcium value below 7.0 mg/dL (7.6% PARSABIV, 3.1% placebo), below 7.5 mg/dL (27% PARSABIV, 5.5% placebo), and below 8.3 mg/dL (79% PARSABIV, 19% placebo). In the combined placebo-controlled studies, 1% of patients in the PARSABIV group and 0% of patients in the placebo group discontinued treatment due to an adverse reaction attributed to a low corrected serum calcium.

Hypophosphatemia

In the combined placebo-controlled studies, 18% of patients treated with PARSABIV and 8.2% of patients treated with placebo had at least one measured phosphorus level below the lower normal limit (i.e., 2.2 mg/dL).

QTc Interval Prolongation Secondary to Hypocalcemia

In the combined placebo-controlled studies, more patients treated with PARSABIV experienced a maximum increase from baseline of greater than 60 msec in the QTcF interval (0% placebo versus 1.2% PARSABIV). The patient incidence of maximum post-baseline predialysis QTcF > 500 msec in the placebo and PARSABIV groups was 1.9% and 4.8%, respectively.

Hypersensitivity

In the combined placebo-controlled studies, the subject incidence of adverse reactions potentially related to hypersensitivity was 4.4% in the PARSABIV group and 3.7% in the placebo group. Hypersensitivity reactions in the PARSABIV group were pruritic rash, urticaria, and face edema.

6.2 Immunogenicity

As with all peptide therapeutics, there is potential for immunogenicity. The detection of anti-drug binding antibody formation is highly dependent on the sensitivity and specificity of the assay. Additionally, the observed incidence of antibody positivity in an assay may be influenced by several factors, including assay methodology, sample handling, timing of sample collection, concomitant medications, and underlying disease. For these reasons, comparison of the incidence of antibodies to etelcalcetide with the incidence of antibodies to other products may be misleading.

In clinical studies, 7.1% (71 out of 995) of patients with secondary hyperparathyroidism treated with PARSABIV for up to 6 months tested positive for binding anti-etelcalcetide antibodies. Fifty-seven out of 71 had pre-existing anti-etelcalcetide antibodies. No evidence of altered pharmacokinetic profile, clinical response, or safety profile was associated with pre-existing or developing anti-etelcalcetide antibodies.

6.3 Postmarketing Experience

The following adverse reactions have been identified during postmarketing use of PARSABIV. Because postmarketing reporting of adverse reactions is voluntary and from a population of uncertain size, it is not always possible to reliably estimate their frequency or establish a causal relationship to drug exposure.

- Anaphylactic reaction
- Hypocalcemia in patients who were administered etelcalcetide concomitantly with other products known to lower serum calcium (e.g. cinacalcet, denosumab)
- Seizures secondary to hypocalcemia

8 USE IN SPECIFIC POPULATIONS

8.1 Pregnancy

Risk Summary

There are no available data on the use of PARSABIV in pregnant women. In animal reproduction studies, effects were seen at doses associated with maternal toxicity that included hypocalcemia. In a pre- and post-natal study in rats administered etelcalcetide during organogenesis through delivery and weaning, there was a slight increase in perinatal pup mortality, delay in parturition, and transient effects on pup growth at exposures 1.8 times the human exposure for the clinical dose of 15 mg three times per week. There was no effect on sexual maturation, neurobehavioral, or reproductive function in the rat offspring. In embryo-fetal studies, when rats and rabbits were administered etelcalcetide during organogenesis, reduced fetal growth was observed at exposures 2.7 and 7 times exposures for the clinical dose, respectively.

The estimated background risk of major birth defects and miscarriage for the indicated population is unknown. In the U.S. general population, the estimated background risk of major birth defects and miscarriage in clinically recognized pregnancies is 2-4% and 15-20%, respectively.

Data

Animal Data

There were no effects on embryo-fetal development in Sprague-Dawley rats when etelcalcetide was dosed at 0.75, 1.5, and 3 mg/kg/day by the intravenous route during organogenesis (pre-mating to gestation day 17) at exposures up to 1.8 times human exposures at the clinical dose of 15 mg three times per week based on AUC. No effects on embryo-fetal development were observed in New Zealand White rabbits at doses of etelcalcetide of 0.375, 0.75, and 1.5 mg/kg by the intravenous route (gestation day 7 to 19), representing up to 4.3 times human exposures based on AUC. In separate studies at higher doses of 4.5 mg/kg in rats (gestation days 6 to 17) and 2.25 mg/kg in rabbits (gestation days 7 to 20), representing 2.7- and 7-fold clinical exposures, respectively, there was reduced fetal growth associated with maternal toxicities of hypocalcemia, tremoring, and reductions in body weight and food consumption.

In a pre- and post-natal development study in Sprague-Dawley rats administered etelcalcetide at 0.75, 1.5, and 3 mg/kg/day by the intravenous route (gestation day 7 to lactation day 20), there was a slight increase in perinatal pup mortality, delay in parturition, and transient reductions in post-natal growth at 3 mg/kg/day (representing 1.8-fold human exposures at the clinical dose of 15 mg three times per week based on AUC), associated with maternal toxicities of hypocalcemia, tremoring, and reductions in body weight and food consumption. There were no effects on sexual maturation, neurobehavioral, or reproductive function at up to 3 mg/kg/day, representing exposures up to 1.8-fold human exposure based on AUC.

8.2 Lactation

Risk Summary

There are no data regarding the presence of PARSABIV in human milk or effects on the breastfed infant or on milk production. Studies in rats showed [^14C]-etelcalcetide was present in the milk at concentrations similar to plasma. Because of the potential for PARSABIV to cause adverse effects in breastfed infants including hypocalcemia, advise women that use of PARSABIV is not recommended while breastfeeding.

Data

Presence in milk was assessed following a single intravenous dose of [^14C]-etelcalcetide in lactating rats at maternal exposures similar to the exposure at the human clinical dose of 15 mg three times per week. [^14C]-etelcalcetide-derived radioactivity was present in milk at levels similar to plasma.

8.4 Pediatric Use

The safety and efficacy of PARSABIV have not been established in pediatric patients.

8.5 Geriatric Use

Of the 503 patients in placebo-controlled studies who received PARSABIV, 177 patients (35.2%) were ≥ 65 years old and 72 patients (14%) were ≥ 75 years old. No clinically significant differences in safety or efficacy were observed between patients ≥ 65 years and younger patients (≥ 18 and < 65 years old). No differences in plasma concentrations of etelcalcetide were observed between patients ≥ 65 years and younger patients (≥ 18 and < 65 years old).

10 OVERDOSAGE

There is no clinical experience with PARSABIV overdosage. Overdosage of PARSABIV may lead to hypocalcemia with or without clinical symptoms and may require treatment. Although PARSABIV is cleared by dialysis, hemodialysis has not been studied as a treatment for PARSABIV overdosage. In the event of overdosage, corrected serum calcium should be checked and patients should be monitored for symptoms of hypocalcemia, and appropriate measures should be taken [see Warnings and Precautions (5.1)].

11 DESCRIPTION

PARSABIV (etelcalcetide) is a synthetic peptide calcium-sensing receptor agonist. Etelcalcetide is a white to off-white powder with a molecular formula of C38H73N21O10S2∙xHCl (4 ≤ x ≤ 5) and a molecular weight of 1047.5 g/mol (monoisotopic; free base). It is soluble in water. The hydrochloride salt of etelcalcetide is described chemically as N-acetyl-D-cysteinyl-S-(L-cysteine disulfide)-D-alanyl-D-arginyl-D-arginyl-D-arginyl-D-alanyl-D-argininamide hydrochloride.

PARSABIV (etelcalcetide) injection is supplied in a single-dose vial containing 5 mg/mL of etelcalcetide as a sterile, preservative-free, ready-to-use clear and colorless solution for intravenous injection.

Each PARSABIV single-dose vial contains 2.5 mg etelcalcetide (equivalent to 2.88 mg etelcalcetide as hydrochloride salt) or 5 mg etelcalcetide (equivalent to 5.77 mg etelcalcetide as hydrochloride salt) or 10 mg etelcalcetide (equivalent to 11.54 mg etelcalcetide as hydrochloride salt). PARSABIV single-dose vial is formulated with 0.85% (w/v) sodium chloride, 10 mM succinic acid, and adjusted to pH 3.3 with sodium hydroxide and/or hydrochloric acid.

12 CLINICAL PHARMACOLOGY

12.1 Mechanism of Action

Etelcalcetide is a calcimimetic agent that allosterically modulates the calcium-sensing receptor (CaSR). Etelcalcetide binds to the CaSR and enhances activation of the receptor by extracellular calcium. Activation of the CaSR on parathyroid chief cells decreases PTH secretion.

12.2 Pharmacodynamics

Following a single intravenous bolus administration of etelcalcetide, PTH levels decreased within 30 minutes post-dose. In the single-dose study, the extent and duration of the reduction in PTH increased with increasing dose. Reduction in PTH levels correlated with plasma etelcalcetide concentrations in hemodialysis patients. The reduction in PTH resulted in reductions in calcium and attenuation of post-dialytic phosphate elevation. The effect of reducing PTH levels was maintained throughout the 6-month dosing period when etelcalcetide was administered by intravenous bolus three times a week.

12.3 Pharmacokinetics

The pharmacokinetics of etelcalcetide is linear and does not change over time following single (5 to 60 mg) and multiple intravenous doses (2.5 to 20 mg) in chronic kidney disease patients with secondary hyperparathyroidism requiring hemodialysis. Etelcalcetide exhibited tri-exponential decay following intravenous administration. Based on population pharmacokinetic analysis, following three times a week intravenous dosing at the end of each 3- to 6-hour hemodialysis session in chronic kidney disease patients, etelcalcetide plasma levels reached steady state in 7-8 weeks after dosing with a predicted accumulation ratio of 3- to 4-fold, and the effective half-life was 3 to 4 days.

Distribution

In the population pharmacokinetics model, volume of distribution at steady state (Vss) was approximately 796 L. Etelcalcetide is predominately bound to plasma albumin by reversible covalent binding. Non-covalent binding of etelcalcetide to plasma proteins is low with a fraction unbound ratio of 0.53. The ratio of blood-to-plasma [^14C]-etelcalcetide concentrations is approximately 0.6.

Elimination

Metabolism

Etelcalcetide is not metabolized by CYP450 enzymes. Etelcalcetide is biotransformed in blood by reversible disulfide exchange with endogenous thiols to predominantly form conjugates with serum albumin. Following a single radiolabeled dose of etelcalcetide in chronic kidney disease patients with secondary hyperparathyroidism requiring hemodialysis, the plasma exposure of biotransformation products is approximately 5-fold higher than that of etelcalcetide and their concentration-time course parallels that of etelcalcetide.

Excretion

Etelcalcetide is cleared by renal excretion in patients with normal renal function, while hemodialysis is the predominant elimination pathway in chronic kidney disease patients requiring hemodialysis. In chronic kidney disease patients on hemodialysis, etelcalcetide was removed with a hemodialysis clearance value of 7.66 L/hr. Following a single radiolabeled dose of etelcalcetide in chronic kidney disease patients with secondary hyperparathyroidism requiring hemodialysis, approximately 60% of [^14C]-etelcalcetide was recovered in dialysate, and approximately 7% recovered in urine and feces combined over 175 days of collection period.

Specific Populations

Effects of Body Weight, Gender, Race, and Age

Results of population pharmacokinetic analyses indicate that body weight (29 to 163 kg), gender, race, and age (20 to 93 years of age) do not influence the pharmacokinetics of etelcalcetide. The pharmacokinetics of etelcalcetide in patients ≥ 65 years of age and in patients < 65 years of age is similar.

Drug Interactions

In Vitro Assessment of Drug Interactions

Etelcalcetide did not inhibit or induce CYP450 enzymes, and is not a substrate of CYP450 enzymes. Etelcalcetide was not a substrate of efflux and uptake transporter proteins (P-glycoprotein [Pgp], breast cancer resistance protein [BCRP], organic anion transporter [OAT] 1 and 3, organic anion polypeptide transporter [OATP] 1B1 and 1B3, organic cation transporter [OCT] 2, and peptide transporter [PEPT] 1 and 2). Etelcalcetide was also not an inhibitor of common transporter proteins (Pgp, BCRP, OAT1, OAT3, OATP1B1, OATP1B3, OCT2, or bile salt export pump [BSEP]).

13 NONCLINICAL TOXICOLOGY

13.1 Carcinogenesis, Mutagenesis, Impairment of Fertility

No drug-related tumors were observed in Tg rasH2 transgenic mice when etelcalcetide was administered at doses of 0.3, 1, and 3 mg/kg in females and 0.375, 0.75, and 1.5 mg/kg in males once daily for 26 weeks by the subcutaneous route, representing up to 0.4-fold clinical exposure at the maximum human dose of 15 mg three times per week based on AUC. Etelcalcetide administration did not produce drug-related tumors when Sprague-Dawley rats were dosed at 0.2, 0.4, 0.8, and 1.6 mg/kg/day by the subcutaneous route for 89 weeks in females and 92 weeks in males, representing up to 0.4-fold clinical exposures achieved in patients receiving etelcalcetide at 15 mg three times per week, based on AUC.

Etelcalcetide was mutagenic in some strains of bacteria (Ames), but was not genotoxic in two in vitro and two in vivo mammalian genotoxicity assays.

There was no effect on male or female fertility when etelcalcetide was dosed at 0.75, 1.5, and 3 mg/kg/day by the intravenous route to rats at exposure levels up to 1.8-fold higher than exposures achieved in patients receiving etelcalcetide at 15 mg three times per week based on AUC.

14 CLINICAL STUDIES

The efficacy and safety of PARSABIV for the treatment of secondary hyperparathyroidism in patients with chronic kidney disease receiving hemodialysis three times per week were evaluated in two 26-week, randomized, double-blind, placebo-controlled studies (Study 1 and Study 2).

The starting dose of PARSABIV was 5 mg three times per week administered at the end of hemodialysis. PARSABIV dose was titrated every 4 weeks until week 17 to a maximum dose of 15 mg three times per week to target a PTH level of less than or equal to 300 pg/mL. PARSABIV was suspended temporarily if two consecutive PTH levels were less than 100 pg/mL. The dose of PARSABIV was not increased if PTH levels were less than or equal to 300 pg/mL, corrected serum calcium was less than 8.3 mg/dL, symptomatic hypocalcemia occurred, or the investigator judged that no dose increase was needed.

The average dose of PARSABIV at the time of the efficacy assessment (weeks 20 through 27, inclusive) was 7.2 mg three times per week. Patients with lower screening PTH levels were on lower doses with a mean average dose of 5.7 mg, 7.4 mg, and 8.7 mg three times per week for patients with screening PTH levels less than 600 pg/mL, 600 to less than or equal to 1000 pg/mL, and greater than 1000 pg/mL, respectively. Throughout the study, patients were maintained on a dialysate calcium concentration of greater than or equal to 2.25 meq/L.

In each study, the primary outcome measure was the proportion of patients with a greater than 30% reduction in PTH levels from baseline to the efficacy assessment phase (mean PTH levels for weeks 20 through 27, inclusive). The other outcome measures were the proportion of patients with a mean PTH of less than or equal to 300 pg/mL, percent change from baseline in PTH, corrected serum calcium, and phosphate levels.

Study 1 enrolled 508 patients (254 PARSABIV, 254 placebo). Baseline demographic and disease characteristics were balanced between groups. The mean age of the patients was 58 years, and 57% were male. Of enrolled patients, 69% were White, 28% were Black, 2% were Asian, and 13% were Hispanic/Latino in ethnicity. The mean baseline PTH level was 834.2 pg/mL, the mean baseline corrected serum calcium was 9.6 mg/dL, and the average duration of hemodialysis prior to study entry (minimum to maximum) was 5.5 (0.1 to 32.2) years. Sixty-six percent of patients had a mean screening PTH level greater than or equal to 600 pg/mL, 74% patients were receiving vitamin D sterols, and 84% patients were receiving phosphate binders.

Study 2 enrolled 515 patients (255 PARSABIV, 260 placebo). Baseline demographic and disease characteristics were balanced between groups. The mean age of the patients was 59 years, and 64% were male. Of enrolled patients, 65% were White, 28% were Black, 4% were Asian, and 13% were Hispanic/Latino in ethnicity. The mean baseline PTH level was 848.4 pg/mL, the mean baseline corrected serum calcium was 9.7 mg/dL, and the average duration of hemodialysis prior to study entry (minimum to maximum) was 5.4 (0.3 to 32.1) years. Sixty-seven percent of patients had a mean screening PTH level greater than or equal to 600 pg/mL, 62% patients were receiving vitamin D sterols, and 81% patients were receiving phosphate binders.

In both studies, a significantly higher proportion of patients treated with PARSABIV achieved a greater than 30% reduction in PTH levels from baseline to the efficacy assessment phase (mean PTH levels for weeks 20 through 27, inclusive) than the proportion of patients treated with placebo. In both studies, reduction in mean PTH, corrected serum calcium, and serum phosphate levels from baseline to the end of study were observed in the PARSABIV arm, and differences between PARSABIV and placebo were statistically significant. Results for each individual study are shown in Table 3.

Table 3: Effects of PARSABIV on Parathyroid Hormone, Corrected Serum Calcium, and Serum Phosphate Measured at Weeks 20 to 27 in Two 6-Month, Placebo-Controlled Studies in Chronic Kidney Disease Patients with Secondary Hyperparathyroidism on Hemodialysis
 | Study 1 |  | Study 2
 | PARSABIV (N = 254) | Placebo (N = 254) | PARSABIV (N = 255) | Placebo (N = 260)
Parathyroid Hormone
Baseline (pg/mL):
Median | 706 | 706 | 740 | 726
Mean (SE) | 849 (33) | 820 (24) | 845 (29) | 852 (34)
Mean EAP (pg/mL) (SE) [Results from a multiple imputation method for missing data using information from patients who discontinued treatment but had final assessment during the EAP. For Study 1, the percentages of patients with no PTH assessment during the EAP were 10% and 14% for PARSABIV and placebo, respectively; for Study 2, they were 11% and 9%, respectively. The corresponding percentages were the same for corrected serum calcium and one to two percentage points higher for serum phosphate.] | 424 (37) | 898 (34) | 416 (32) | 971 (46)
Mean Percent Change, % (SE) [Other outcome measures for Studies 1 and 2.] , | -49.4 (3.4) [p < 0.001 vs. placebo] | 14.9 (3.6) | -47.8 (3.7) | 18.6 (3.5)
Patients with > 30% Reduction in PTH during the EAP, multiple imputation, n (%) [Main outcome measure for Studies 1 and 2.] , | 196 (77) | 28 (11) | 201 (79) | 29 (11)
Patients with ≤ 300 pg/mL in PTH during the EAP, n (%), | 131 (52) | 16 (6) | 142 (56) | 14 (5)
Corrected Serum Calcium
Mean Baseline (mg/dL) (SE) | 9.7 (0.04) | 9.6 (0.04) | 9.6 (0.04) | 9.7 (0.04)
Mean EAP (mg/dL) (SE) | 9.0 (0.1) | 9.7 (0.04) | 9.0 (0.1) | 9.7 (0.05)
Mean Percent Change, % (SE), | -7.0 (0.6) | 0.9 (0.6) | -7.0 (0.7) | -0.8 (0.6)
Serum Phosphate
Mean Baseline (mg/dL) (SE) | 6.0 (0.1) | 5.8 (0.1) | 5.8 (0.1) | 5.8 (0.1)
Mean EAP (mg/dL) (SE) | 5.4 (0.1) | 5.5 (0.1) | 5.2 (0.1) | 5.6 (0.1)
Mean Percent Change, % (SE), | -8.8 (2.5) [p = 0.08 vs. placebo] | -3.6 (2.8) | -7.2 (2.5) [p < 0.01 vs. placebo] | -0.3 (2.2)
EAP = Efficacy Assessment Phase; weeks 20 through 27, inclusive

PARSABIV decreased PTH levels regardless of baseline PTH, duration of dialysis, whether or not patients had been previously treated with cinacalcet, and whether or not patients were receiving vitamin D sterols. Reductions in PTH levels, corrected serum calcium, and serum phosphate were maintained for up to 78 weeks of treatment in those patients who elected to participate in the extension phase of both studies.

16 HOW SUPPLIED/STORAGE AND HANDLING

PARSABIV (etelcalcetide) injection is supplied in a single-dose vial (type I glass) with stopper (fluoropolymer laminated elastomeric) and an aluminum seal with flip-off dust cover containing 5 mg/mL of etelcalcetide as a ready-to-use clear and colorless solution in the following strengths:

2.5 mg/0.5 mL | Carton of 10 single-dose vials | NDC 55513-740-10 NDC 55513-740-20
5 mg/mL | Carton of 10 single-dose vials | NDC 55513-741-10 NDC 55513-741-20
10 mg/2 mL | Carton of 10 single-dose vials | NDC 55513-742-10 NDC 55513-742-20

Storage

Store in the original carton in refrigerator at 2°C to 8°C (36°F to 46°F) to protect from light. Once removed from the refrigerator:

- Do not expose to temperatures above 25°C (77°F).
- Use within 7 days if stored in the original carton.
- Use within 4 hours and do not expose to direct sunlight if removed from the original carton.

17 PATIENT COUNSELING INFORMATION

Hypocalcemia

Advise patients to report symptoms of hypocalcemia, including paresthesias, myalgias, muscle spasms, and seizures, to their healthcare provider [see Warnings and Precautions (5.1)].

Heart Failure

Advise patients with heart failure that use of PARSABIV may worsen their heart failure and additional monitoring may be required [see Warnings and Precautions (5.2)].

Upper Gastrointestinal Bleeding

Advise patients to report any symptoms of upper gastrointestinal bleeding to their healthcare provider [see Warnings and Precautions (5.3)].

Laboratory Monitoring

Inform patients of the importance of regular blood tests, in order to monitor the safety and efficacy of PARSABIV therapy.

Lactation

Advise women that use of PARSABIV is not recommended while breastfeeding [see Use in Specific Populations (8.2)].

PARSABIV® (etelcalcetide)

Manufactured for:
KAI Pharmaceuticals, Inc., a wholly owned subsidiary of Amgen, Inc.
One Amgen Center Drive
Thousand Oaks, California 91320-1799
Patent: http://pat.amgen.com/Parsabiv/
© 2017-2025 Amgen, Inc. All rights reserved.
V5

PRINCIPAL DISPLAY PANEL - 2.5 mg/0.5 mL Vial Carton

10 x 0.5 mL Single-dose Vials
NDC 55513-740-10

AMGEN®

Parsabiv®
(etelcalcetide)
Injection

2.5 mg/
0.5 mL

For Intravenous Use after Hemodialysis
Single-dose vial. Discard unused portion
Store at 2°C to 8°C (36°F to 46°F) in the original carton in order to
protect from light.
Sterile, preservative-free solution

Rx Only

PRINCIPAL DISPLAY PANEL - 5 mg/mL Vial Carton

10 x 1 mL Single-dose Vials
NDC 55513-741-10

AMGEN®

Parsabiv®
(etelcalcetide)
Injection

5
mg/mL

For Intravenous Use after Hemodialysis
Single-dose vial. Discard unused portion
Store at 2°C to 8°C (36°F to 46°F) in the original carton in order to
protect from light.
Sterile, preservative-free solution

Rx Only

PRINCIPAL DISPLAY PANEL - 10 mg/2 mL Vial Carton

10 x 2 mL Single-dose Vials
NDC 55513-742-10

AMGEN®

Parsabiv®
(etelcalcetide)
Injection

10 mg/
2 mL

For Intravenous Use after Hemodialysis
Single-dose vial. Discard unused portion
Store at 2°C to 8°C (36°F to 46°F) in the original carton in order to
protect from light.
Sterile, preservative-free solution

Rx Only